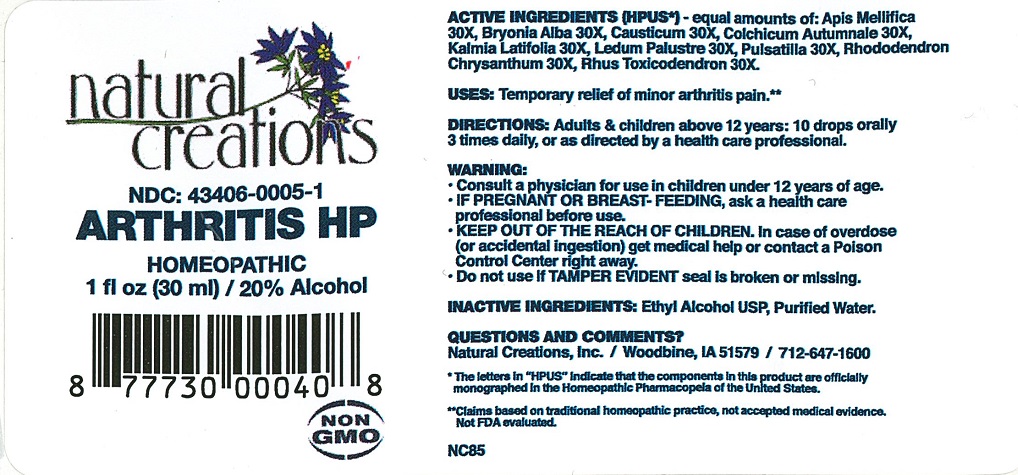 DRUG LABEL: Arthritis HP
NDC: 43406-0005 | Form: LIQUID
Manufacturer: Natural Creations, Inc.
Category: homeopathic | Type: HUMAN OTC DRUG LABEL
Date: 20251113

ACTIVE INGREDIENTS: APIS MELLIFERA 30 [hp_X]/1 mL; BRYONIA ALBA ROOT 30 [hp_X]/1 mL; CAUSTICUM 30 [hp_X]/1 mL; KALMIA LATIFOLIA LEAF 30 [hp_X]/1 mL; LEDUM PALUSTRE TWIG 30 [hp_X]/1 mL; PULSATILLA VULGARIS 30 [hp_X]/1 mL; RHODODENDRON AUREUM LEAF 30 [hp_X]/1 mL; TOXICODENDRON PUBESCENS LEAF 30 [hp_X]/1 mL
INACTIVE INGREDIENTS: WATER; ALCOHOL

Arthritis HP

ACTIVE INGREDIENT

Active Ingredients (HPUS*): Apis Mellifica 30X, Bryonia Alba 30X, Causticum 30X, Colchicum Autumnale 30X, Kalmia Latifolia 30X, Ledum Palustre 30X, Pulsatilla 30X, Rhododendron Chrysanthum 30X, Rhus Toxicodendron 30X

INDICATIONS AND USAGE

USES: Temporarily relief of minor arthritis pain.**

WARNING:

Consult a physician for use in children under 12 years of age. IF PREGNANT OR BREAST-FEEDING, ask a health care professional before use. KEEP OUT OF THE REACH OF CHILDREN. In case of overdose, (or accidental ingestion) get medical help or contact a Poison Control Center right away.

DOSAGE AND ADMINISTRATION

DIRECTIONS: Audlts and children above 12 years: 10 drops orally 3 times daily, or as directed by a health care professional.

OTHER INFORMATION: Tamper Seal: "Sealed for your protection."

Do not use if seal is broken or missing.

REFERENCES

*The letters "HPUS" indicate the components in the product are officially monographed in the Homeopathic Pharmacopeia of the United States.

**Claims based on traditional homeopathic practice, not accepted medical evidence. Not FDA evaluated.

INACTIVE INGREDIENTS: Purified Water, USP Ethanol Alcohol 20%

QUESTIONS AND COMMENTS?

Natural Creations / Woodbine, IA 51579 / 712-647-1600

PURPOSE

USES: Temporarily relief of minor arthritis pain.**

KEEP OUT OF REACH OF CHILDREN. In case of overdose (or accidental ingestion) get medical help or contact a Poison Control Center.

PACKAGE LABEL

NDC: 43406-0005-1

ARTHRITIS HP

HOMEOPATHIC

1 fl oz (30 mL) / 20% Alcohol